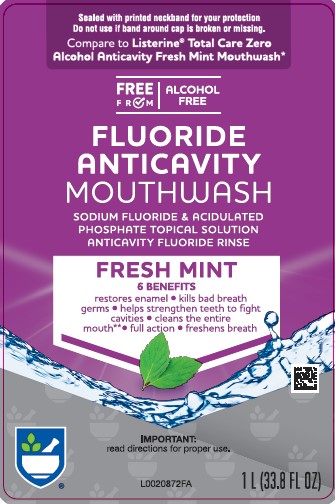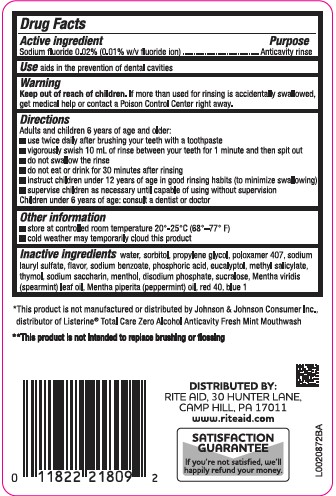 DRUG LABEL: Anticavity
NDC: 11822-9718 | Form: RINSE
Manufacturer: Rite Aid Corporation
Category: otc | Type: HUMAN OTC DRUG LABEL
Date: 20260202

ACTIVE INGREDIENTS: SODIUM FLUORIDE 0.2 mg/1 mL
INACTIVE INGREDIENTS: SODIUM LAURYL SULFATE; SODIUM BENZOATE; PHOSPHORIC ACID; EUCALYPTOL; METHYL SALICYLATE; THYMOL; SACCHARIN SODIUM; MENTHOL; SODIUM PHOSPHATE, DIBASIC, ANHYDROUS; SUCRALOSE; SPEARMINT OIL; PEPPERMINT OIL; FD&C RED NO. 40; FD&C BLUE NO. 1; WATER; SORBITOL; PROPYLENE GLYCOL; POLOXAMER 407

Rite Aid 971.001/971AB
Burn-Free Fluoride Anti-Cavity Mouthwash

Active ingredient

Sodium fluoride 0.02% (0.01% w/v fluoride ion)

Purpose

Anticavity rinse

Use

aids in the prevention of dental cavities

Warning

for this product

Keep out of reach of children.

If more than used for rinsing is accidentally swallowed, get medical help or contact a Poison Control Center right away.

Directions

Adults and children 6 years of age and older:

- use twice daily after brushing your teeth with a toothpaste
- vigorously swish 10 mL of rinse between your teeth for 1 minute and then spit out
- do not swallow the rinse
- do not eat or drink for 30 minutes after rinsing
- instruct children under 12 years of age in good rinsing habits (to minimize swallowing)
- supervise children as necessary until capable of using without supervision

Children under 6 years of age: consult a dentist or doctor

Other information

- store at controlled room temperature 20°-25°C (68°–77° F)
- cold weather may temporarily cloud this product

Inactive ingredients

water, sorbitol, propylene glycol, poloxamer 407, sodium lauryl sulfate, flavor, sodium benzoate, phosphoric acid, eucalyptol, methyl salicylate, thymol, sodium saccharin, menthol, disodium phosphate, sucralose, Mentha viridis (spearmint) leaf oil, Mentha piperita (peppermint) oil, red 40, blue 1

Disclaimers

*This product is not manufactured or distributed by Johnson & Johnson Consumer Inc., distributor of Listerine®Total Care Zero Alcohol Anticavity Fresh Mint Mouthwash.

**This product is not intended to replace brushing or flossing.

ADVERSE REACTION

Distributed by:

Rite Aid 30 Hunter Lane,

Camp Hill, PA 17011

www.riteaid.com

SATISFACTION GUARANTEE

If you're not satisifed, we'll happily refund your money.

Principal Panel Display

Sealed with printed neckband for your protection

Do not use if band around cap is broken or missing.

Compare to Listerine®Total Care Zero Alcohol Anticavity Fresh Mint Mouthwash*

FREE FROM

ALCOHOL FREE

Fluoride AntiCavity Mouthwash

Sodium Fluoride & Acidulated

Phosphate Topical Solution

Anticavity Fluoride Rinse

Fresh Mint

6 Benefits

- Restores enamel
- Kills bad breath germs
- Helps strengthen teeth to fight cavities
- Cleans the entire mouth**
- Full action
- Freshens breath

Important: read directions for proper use.

1 L (33.8 FL OZ)